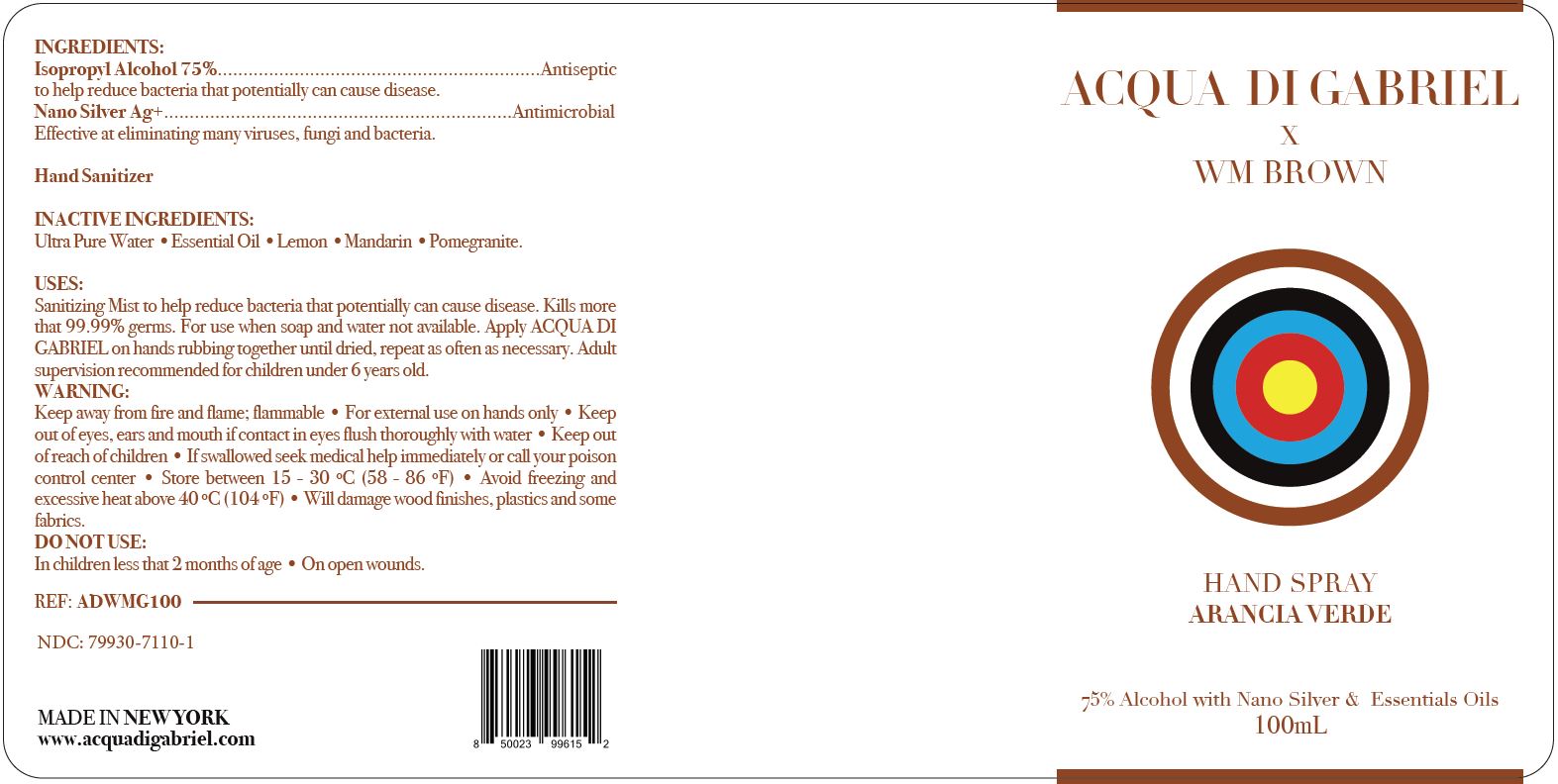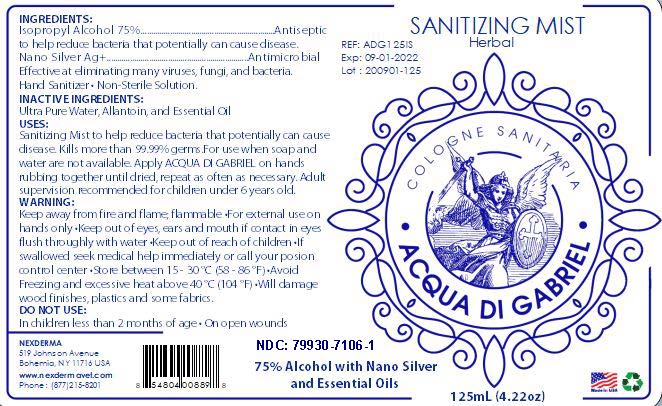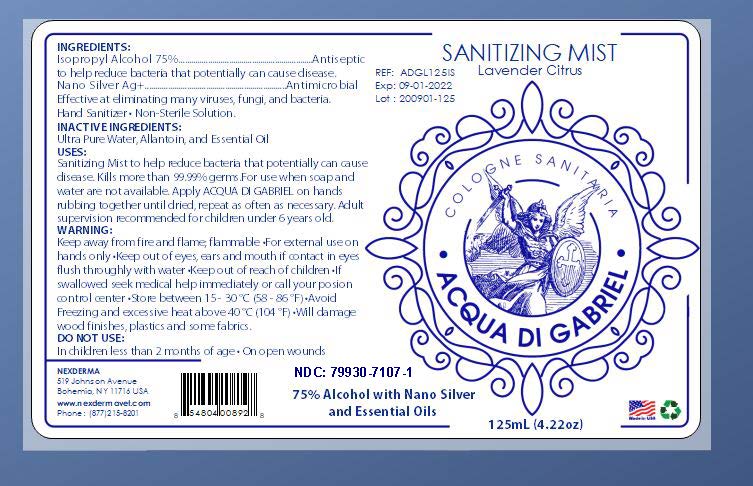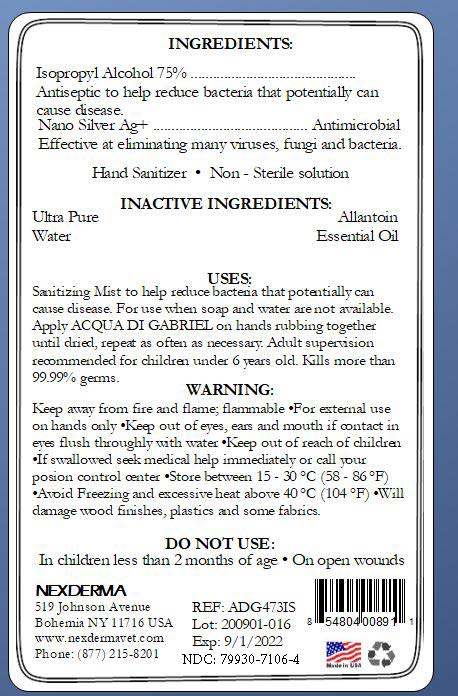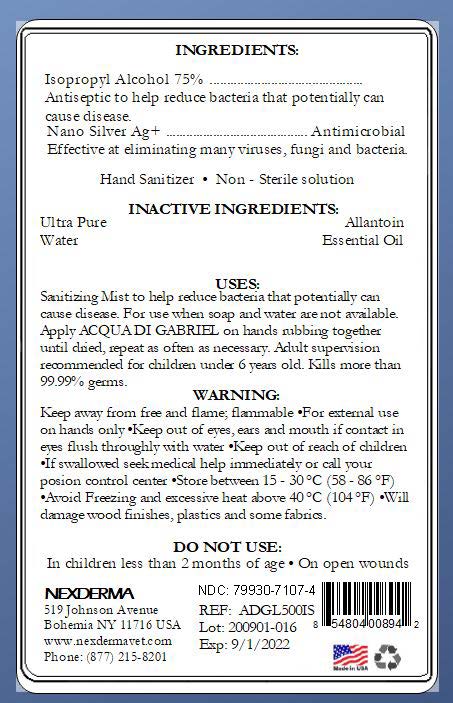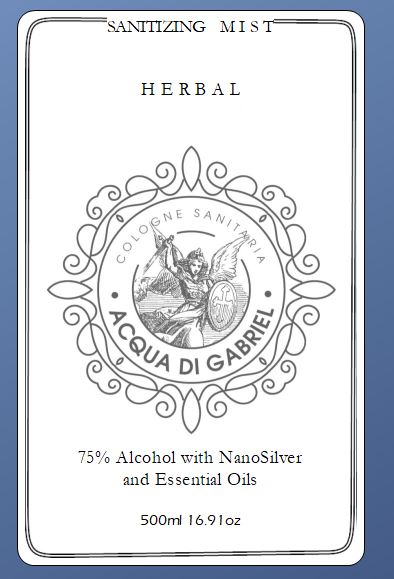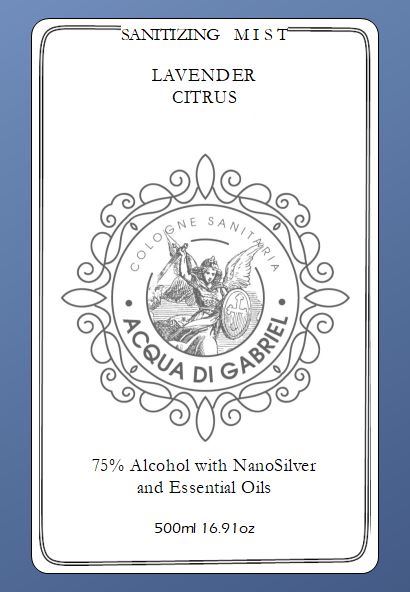 DRUG LABEL: WM Brown x Acqua Di Gabriel
NDC: 79930-7110 | Form: SPRAY
Manufacturer: Nexderma
Category: otc | Type: HUMAN OTC DRUG LABEL
Date: 20201019

ACTIVE INGREDIENTS: ISOPROPYL ALCOHOL 75 mL/100 mL
INACTIVE INGREDIENTS: ALLANTOIN 0.03 mL/100 mL; SILVER 0.5 mL/100 mL; WATER; POMEGRANATE SEED OIL; LEMON OIL; MANDARIN OIL

Acqua Di Gabriel ISO Version

Active Ingredient(s)

Isopropyl Alcohol 75% v/v. Purpose: Antiseptic

Inactive ingredients

Allantoin
Ultra Pure Water
Silver

Use

Hand Sanitizer to help reduce bacteria that potentially can cause disease. For use when soap and water are not available.

KEEP OUT OF REACH OF CHILDREN

Adult supervision recommended for children under 6 years old.

Warnings

Keep away form fire and flame.
Flammable
For external use on hands only.
Keep out of eye, ears and mouth.
If contact in eyes, flush thoroughly with water.
Keep out of reach of children.
If swallowed seek medical help immediately or call your poison control center.
Store between 15-30 (58-86F)
Avoid freezing and excessive heat above 40C (104F)
Will damage wood finishes, plastics and some fabrics.

Do not use

- in children less than 2 months of age
- on open skin wounds

Directions

- Dosage: Place enough product on hands to cover all surfaces. Rub hands together until dry.
- Administration:Topoical

Purpose

Purpose: to help reduce bacteria that potentially can cause disease. For use when soap and water are not available.

Package Label - Principal Display Panel

125 ml NDC: 79930-7106-1

500 ml NDC: 79930-7106-4

125 ml NDC: 79930-7107-1 Lavender Citrus

500 ml NDC: 79930-7107-4 Lavender Citrus

100 ml NDC: 79930-7110-1 WM Brown LMP